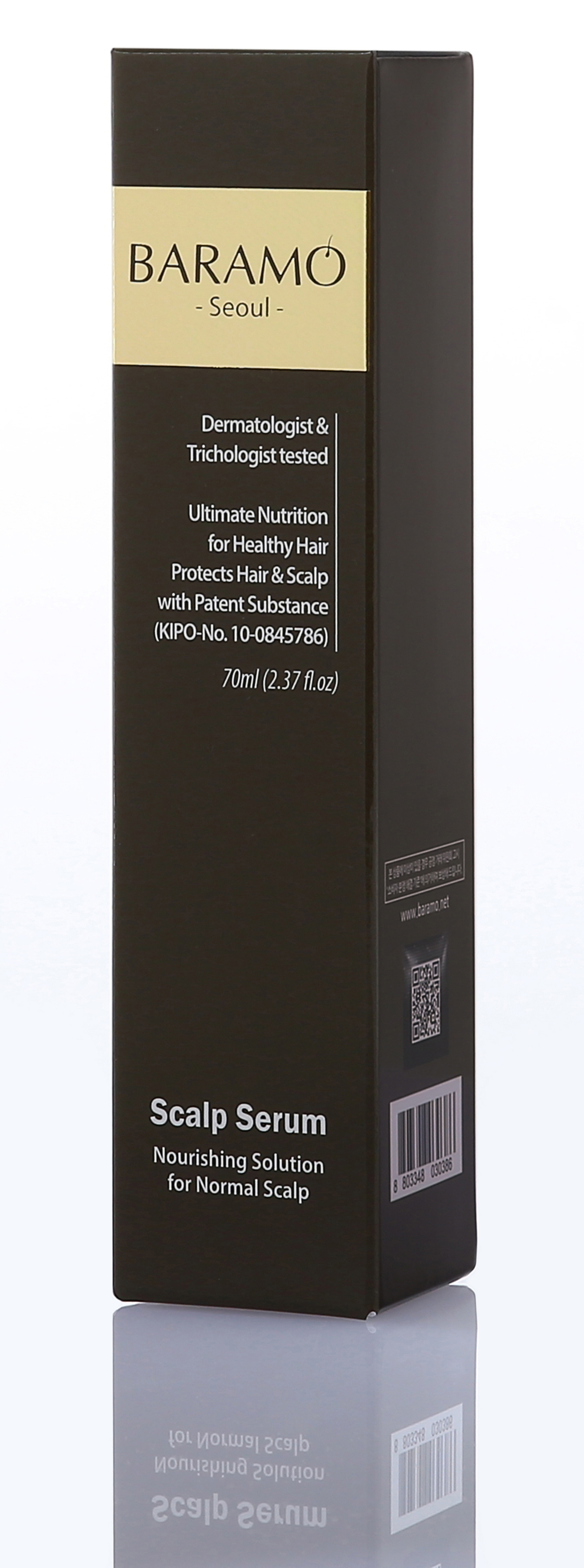 DRUG LABEL: BARAMO Scalp Serum for Normal Scalp
NDC: 69961-050 | Form: SOLUTION
Manufacturer: Mentor Lab
Category: otc | Type: HUMAN OTC DRUG LABEL
Date: 20161024

ACTIVE INGREDIENTS: STYPHNOLOBIUM JAPONICUM FLOWER BUD 0.03 g/70 mL
INACTIVE INGREDIENTS: Water; Glycerin

ACTIVE INGREDIENT

Active Ingredient: Sophora Japonica Bud Extract 0.055%

INACTIVE INGREDIENT

Inactive Ingredients: Water, Alcohol Denat., Glycerin, Butylene Glycol, Ammonium Acryloyldimethyltaurate/VP Copolymer, PEG-60 Hydrogenated Castor Oil, Phenoxyethanol, Propanediol, Caprylyl Glycol, Ethylhexylglycerin, Panthenol, Menthol, Fragrance, Sophora Japonica Bud Extract, Punica Granatum Fruit Extract, Glycine Soja (Soybean) Seed Extract, Coptis Japonica Root Extract, Anemarrhena Asphodeloides Root Extract, Eriobotrya Japonica Leaf Extract, Centella Asiatica Extract, Aloe Barbadensis Leaf Extract, Paeonia Suffruticosa Root Extract, Scutellaria Baicalensis Root Extract, Allantoin, Hydroxyethylcellulose, Adenosine, 1,2-Hexanediol, Hyaluronic Acid.

PURPOSE

Purpose: strengthens & protects hair and scalp

WARNINGS

Warnings: 1. Stop using the product if the following problems arise while using the product as continued use could worsen the symptoms; consult with a dermatologist. 2. Do not use on areas with wounds, eczema, and dermatitis. 3. Storage and handling precautions. 4. Wash off the product if it gets in the eye. 5. Keep out of reach of children. 6. Store in a cool, dry place away from direct sunlight. 7. External use only.

KEEP OUT OF REACH OF CHILDREN

Direction

Direction: -For best use, use BARAMO Scalp Serum twice of daily after cleans your hair. It helps your scalp get healthy and strong through the day and the night. -Apply to dry scalp & gently massage on problematic area. -Leave on your scalp. -Do not rinse off. -Condition your hair with BARAMO Hair Essence for silky hair.

Direction

Direction: -For best use, use BARAMO Scalp Serum twice of daily after cleans your hair. It helps your scalp get healthy and strong through the day and the night. -Apply to dry scalp & gently massage on problematic area. -Leave on your scalp. -Do not rinse off. -Condition your hair with BARAMO Hair Essence for silky hair.